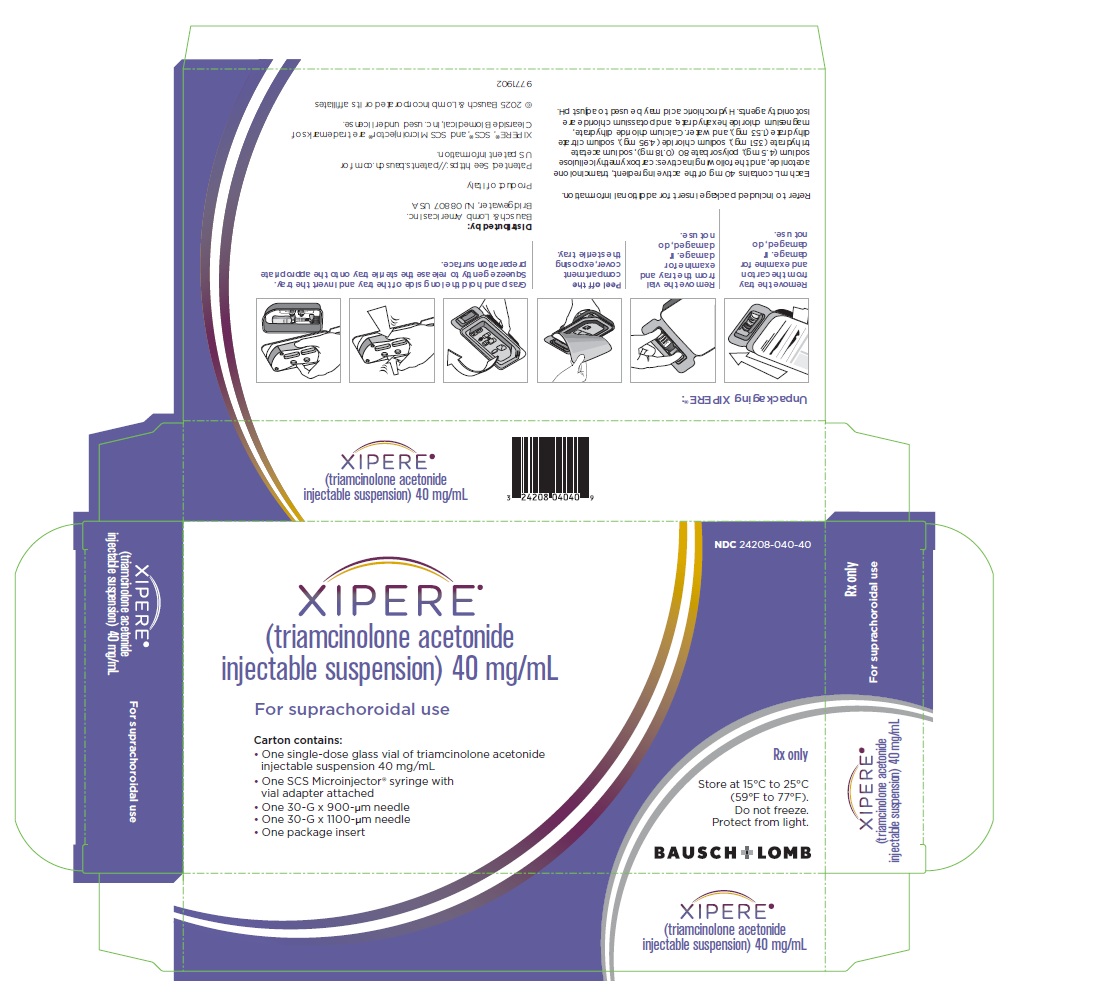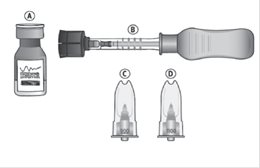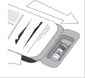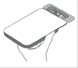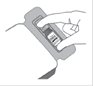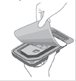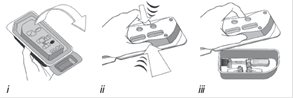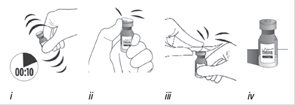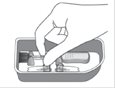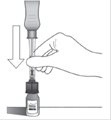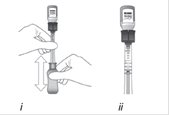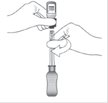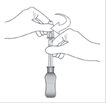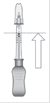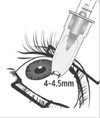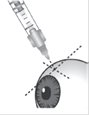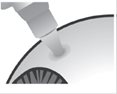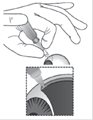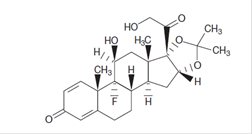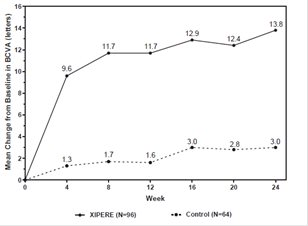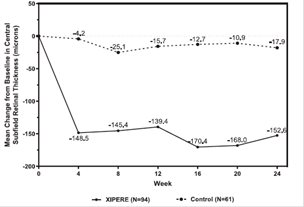 DRUG LABEL: Xipere
NDC: 24208-040 | Form: INJECTION, SUSPENSION
Manufacturer: Bausch & Lomb Incorporated
Category: prescription | Type: HUMAN PRESCRIPTION DRUG LABEL
Date: 20251008

ACTIVE INGREDIENTS: TRIAMCINOLONE ACETONIDE 40 mg/1 mL
INACTIVE INGREDIENTS: POLYSORBATE 80; SODIUM CHLORIDE; POTASSIUM CHLORIDE; CALCIUM CHLORIDE; MAGNESIUM CHLORIDE; SODIUM ACETATE; TRISODIUM CITRATE DIHYDRATE; HYDROCHLORIC ACID; WATER; CARBOXYMETHYLCELLULOSE SODIUM, UNSPECIFIED

HIGHLIGHTS OF PRESCRIBING INFORMATION

These highlights do not include all the information needed to use XIPERE®safely and effectively. See full prescribing information for XIPERE®.
XIPERE®(triamcinolone acetonide injectable suspension), for suprachoroidal use
Initial U.S. Approval: 1957

1 INDICATIONS AND USAGE

XIPERE®is a corticosteroid indicated for the treatment of macular edema associated with uveitis. (1)

2 DOSAGE AND ADMINISTRATION

The recommended dosage is 4 mg (0.1 mL) administered as a suprachoroidal injection. (2.1)

3 DOSAGE FORMS AND STRENGTHS

Injectable suspension: triamcinolone acetonide 40 mg/mL in a single-dose vial. (3)

4 CONTRAINDICATIONS

- Ocular or periocular infections (4.1)
- Hypersensitivity to triamcinolone or any component of this product (4.2)

5 WARNINGS AND PRECAUTIONS

Potential Corticosteroid-Related Effects: Use of corticosteroids may produce cataracts, increased intraocular pressure, and glaucoma. (5.1)

6 ADVERSE REACTIONS

In controlled studies, the most common adverse reactions reported by ≥ 10% of patients and at a rate greater than control included elevated intraocular pressure and eye pain. (6.1)

To report SUSPECTED ADVERSE REACTIONS, contact Bausch & Lomb Incorporated at 1-800-553-5340 or FDA at 1-800-FDA-1088 or www.fda.gov/medwatch.

FULL PRESCRIBING INFORMATION

1 INDICATIONS AND USAGE

XIPERE®(triamcinolone acetonide injectable suspension) 40 mg/mL is indicated for the treatment of macular edema associated with uveitis.

2 DOSAGE AND ADMINISTRATION

2.1 Dosing Information

For suprachoroidal injection using the SCS Microinjector®. The recommended dose of XIPERE®is 4 mg (0.1 mL of the 40 mg/mL injectable suspension).

2.2 Preparation for Administration

Suprachoroidal injection is performed under aseptic conditions. The components for administration include:

1. One single-dose glass vial of triamcinolone acetonide injectable suspension 40 mg/mL
2. One SCS Microinjector®syringe with vial adapter attached
3. One 30-G x 900-µm needle
4. One 30-G x 1100-µm needle

Step 1

Figure A

Remove the tray from the carton (see Figure A).

The tray consists of two compartments:

- An open, non-sterile compartment that holds the vial
- A sealed compartment that contains a sterile tray

Step 2

Figure B

Examine the tray for damage (see Figure B). Ensure that the sealed compartment cover is intact and that there is no evidence of damage. If damage is present, do not use.

Step 3

Figure C

Remove the vial from the tray (see Figure C). Examine the vial and ensure there is no evidence of damage. Set aside for use in Step 6.

Step 4

Figure D

Peel off the compartment cover, exposing the sterile tray (see Figure D).

Step 5

Figure E

Grasp and hold the long sides of the tray and invert the tray. Squeeze gently to release the sterile tray onto the appropriate sterile preparation surface (see Figure E, i– iii).

Step 6

Figure F

Vigorously shake the vial for 10 seconds. Inspect the vial for clumping or granular appearance of the sterile contents. If clumping or granular appearance is present, do not use. Remove the protective plastic cap from the vial and clean the top of the vial with an alcohol wipe. Place the vial on a flat surface (see Figure F, i– iv). To avoid settling of the suspension, continue to the next steps without delay.

Step 7

Remove the syringe with attached vial adapter from the tray (see Figure G). Ensure the vial adapter is secured to the syringe by tightening the connection.

Figure G

Step 8

Holding the clear barrel of the syringe, connect the vial adapter to the vial by firmly pushing the spike of the vial adapter straight through the center of the vial septum until it snaps securely into place (see Figure H).

NOTE: Do not introduce additional air into the syringe prior to connecting the vial adapter to the vial.

Figure H

Step 9

Figure I

Invert the entire assembly so that the vial is directly above the syringe. Slide the white plunger handle all the way back and forth multiple times to fill the entire syringe with drug and remove any remaining air (see Figure I, iand ii).

NOTE: The syringe should be handled by the clear barrel during filling, connecting and disconnecting procedures. The white plunger handle has a stop to prevent complete removal of the plunger from the syringe.

Step 10

Figure J

While holding the vial adapter and vial, disconnect the syringe by twisting it off of the adapter (see Figure J).

Retain the vial, with the vial adapter connected, in the event re-access is necessary.

Step 11

Figure K

Connect the 900-µm needle to the syringe by twisting onto the syringe (see Figure K). At the discretion of the physician, the longer needle may be used. Ensure a secure connection.

Step 12

Figure L

Hold the syringe barrel with the needle pointing up. Expel air bubbles and excess drug by slowly sliding the white plunger handle so that the plunger tip aligns with the line that marks 0.1 mL on the syringe (see Figure L).

NOTE: Perform the suprachoroidal injection without delay to prevent settling of the drug.

2.3 Administration

The suprachoroidal injection procedure should be carried out under controlled aseptic conditions, which include the use of sterile gloves, a sterile drape, a sterile eyelid speculum (or equivalent), and a sterile cotton swab. Adequate anesthesia and a broad-spectrum microbicide applied to the periocular skin, eyelid, and ocular surface are recommended to be given prior to the suprachoroidal injection.

Step 13

Figure M

Identify the injection site by measuring 4 – 4.5 mm posterior to the limbus using the tip of the needle cap or ophthalmic calipers (see Figure M).

Step 14

Figure N

Carefully pull off the needle cap to expose the needle. Holding the syringe perpendicular to the ocular surface, insert the needle through the conjunctiva into the sclera (see Figure N).

Step 15

Figure O

Once the needle is inserted into the sclera, ensure that the hub of the needle is in firm contact with the conjunctiva, compressing the sclera and creating a dimple on the ocular surface using a light amount of force against the eye. Maintain the dimple and perpendicular positioning throughout the injection procedure (see Figure O).

Step 16

Figure P

While maintaining the dimple on the ocular surface, gently press the white plunger handle so that the plunger moves forward and drug is slowly injected over 5 – 10 seconds. Movement of the plunger will be felt as a loss of resistance and indicates that the needle is in the correct anatomical location for suprachoroidal injection (see Figure P).

If resistance is felt and the plunger does not advance, confirm the hub is in firm contact with the conjunctiva creating a dimple and that the syringe is positioned perpendicular to the ocular surface. Small adjustments in positioning may be necessary.

Step 17

Maintain the hub against the eye for 3 – 5 seconds after the drug product has been injected.

Step 18

Remove the needle slowly from the eye while holding a sterile cotton swab next to the needle as it is withdrawn. Immediately cover the injection site with a sterile cotton swab.

Step 19

Hold the swab over the injection site with light pressure for a few seconds and then remove.

If continued resistance is experienced during injection attempts:

- Remove the needle from the eye and examine the eye for any issues. If patient safety is not at risk, the physician may use medical judgment to restart the injection procedure at a new site adjacent to the original injection site.
- If resistance continues and patient safety is not at risk, the physician may use appropriate medical judgment to change to the additional included needle in the sterile tray. Twist to remove the needle and reconnect the syringe to the vial by twisting the syringe onto the vial adapter. Repeat the preparation and injection process as stated in Steps 9 – 18 with the additional needle (allowing for any partial dose given with the first needle when completing preparation Step 12).

Immediately following suprachoroidal injection, patients should be monitored for elevation of intraocular pressure. Appropriate monitoring may consist of a check for perfusion of the optic nerve head or tonometry.

Following suprachoroidal injection, patients should be instructed to report any symptoms suggestive of endophthalmitis or retinal detachment (e.g., eye pain, redness of eye, photophobia, blurring of vision) without delay [see Patient Counseling Information (17)] .

Each XIPERE®package (microinjector syringe with vial adapter, 900-µm needle, 1100-µm needle, and vial of triamcinolone acetonide injectable suspension 40 mg/mL) is single-dose and should only be used for the treatment of one eye.

After suprachoroidal injection, all drug product and components (used or unused) must be discarded appropriately.

3 DOSAGE FORMS AND STRENGTHS

Injectable suspension: triamcinolone acetonide 40 mg/mL suspension in a single-dose glass vial for use with the supplied SCS Microinjector®.

4 CONTRAINDICATIONS

4.1 Ocular or Periocular Infections

XIPERE®is contraindicated in patients with active or suspected ocular or periocular infections including most viral diseases of the cornea and conjunctiva, including active epithelial herpes simplex keratitis (dendritic keratitis), vaccinia, varicella, mycobacterial infections, and fungal diseases.

4.2 Hypersensitivity

XIPERE®is contraindicated in patients with known hypersensitivity to triamcinolone acetonide or any other components of this product.

5 WARNINGS AND PRECAUTIONS

5.1 Potential Corticosteroid-Related Effects

Use of corticosteroids may produce cataracts, increased intraocular pressure, and glaucoma. Use of corticosteroids may enhance the establishment of secondary ocular infections due to bacteria, fungi, or viruses.

Corticosteroids should be used cautiously in patients with a history of ocular herpes simplex. Corticosteroids should not be used in patients with active ocular herpes simplex.

5.2 Alterations in Endocrine Function

Hypothalamic-pituitary-adrenal (HPA) axis suppression, Cushing’s syndrome, and hyperglycemia can occur following administration of a corticosteroid. Monitor patients for these conditions with chronic use.

Corticosteroids can produce reversible HPA axis suppression with the potential for glucocorticosteroid insufficiency after withdrawal of treatment. Drug induced secondary adrenocortical insufficiency may be minimized by gradual reduction of dosage. This type of relative insufficiency may persist for months after discontinuation of therapy; therefore, in any situation of stress occurring during that period, hormone therapy should be reinstituted. Metabolic clearance of corticosteroids is decreased in hypothyroid patients and increased in hyperthyroid patients. Changes in thyroid status of the patient may necessitate adjustment in dosage.

6 ADVERSE REACTIONS

6.1 Clinical Trials Experience

Because clinical trials are conducted under widely varying conditions, adverse reaction rates observed in the clinical trials of a drug cannot be directly compared to rates in the clinical trials of another drug and may not reflect the rates observed in practice.

XIPERE®was studied in a multicenter, randomized, sham-controlled, double-masked study in patients with macular edema associated with uveitis. Table 1 summarizes data available from the clinical trial for XIPERE®treated patients and control patients.

The most common ocular (study eye) adverse reactions occurring in ≥ 2% of patients and non-ocular adverse reactions occurring in ≥ 5% of patients are shown in Table 1.

Table 1: Ocular Adverse Reactions Reported in ≥ 2% of Patients and Non-ocular Adverse Reactions Reported in ≥ 5% of Patients
Adverse Reaction | XIPERE® (N = 96) n (%) | Control (N = 64) n (%)
Ocular
Increased intraocular pressure, non-acutea, b | 13 (14%) | 9 (14%)
Eye pain, non-acuteb | 11 (12%) | 0
Cataractc | 7 (7%) | 4 (6%)
Increased intraocular pressure, acutea, d | 6 (6%) | 0
Vitreous detachment | 5 (5%) | 1 (2%)
Injection site pain | 4 (4%) | 2 (3%)
Conjunctival haemorrhage | 4 (4%) | 2 (3%)
Visual acuity reduced | 4 (4%) | 1 (2%)
Dry eye | 3 (3%) | 1 (2%)
Eye pain, acuted | 3 (3%) | 0
Photophobia | 3 (3%) | 0
Vitreous floaters | 3 (3%) | 0
Uveitis | 2 (2%) | 7 (11%)
Conjunctival hyperaemia | 2 (2%) | 2 (3%)
Punctate keratitis | 2 (2%) | 1 (2%)
Conjunctival oedema | 2 (2%) | 0
Meibomianitis | 2 (2%) | 0
Anterior capsule contraction | 2 (2%) | 0
Chalazion | 2 (2%) | 0
Eye irritation | 2 (2%) | 0
Eye pruritus | 2 (2%) | 0
Eyelid ptosis | 2 (2%) | 0
Photopsia | 2 (2%) | 0
Vision blurred | 2 (2%) | 0
Non-ocular
Headache | 5 (5%) | 2 (3%)
aIncludes intraocular pressure increased and ocular hypertension
bDefined as not occurring on the day of the injection procedure, or occurring on the day of the injection procedure and not resolving the same day
cIncludes cataract, cataract cortical, and cataract subcapsular
dDefined as occurring on the day of the injection procedure and resolving the same day

8 USE IN SPECIFIC POPULATIONS

8.1 Pregnancy

Risk Summary

There are no adequate and well-controlled studies with XIPERE®in pregnant women to inform drug-associated risks. In animal reproductive studies from the published literature, topical ocular administration of corticosteroids has been shown to produce teratogenicity at clinically relevant doses. There is negligible systemic XIPERE®exposure following suprachoroidal injection [see Clinical Pharmacology (12.3)] . Corticosteroids should be used during pregnancy only if the potential benefit justifies the potential risk to the fetus.

All pregnancies have a background risk of birth defect, loss, or other adverse outcomes. In the U.S. general population, the estimated risk of major birth defects and miscarriage in clinically recognized pregnancies is 2% to 4% and 15% to 20%, respectively.

Animal Data

Animal reproduction studies using XIPERE®have not been conducted. In animal reproductive studies from the published literature, topical ocular administration of corticosteroids to pregnant mice and rabbits during organogenesis has been shown to produce cleft palate, embryofetal death, herniated abdominal viscera, hypoplastic kidneys, and craniofacial malformations.

8.2 Lactation

Risk Summary

It is not known whether ocular administration of corticosteroids could result in sufficient systemic absorption to produce detectable quantities in human milk. Systemically administered corticosteroids appear in human milk and could suppress growth, interfere with endogenous corticosteroid production, or cause other untoward effects. The developmental and health benefits of breastfeeding should be considered along with the mother’s clinical need for XIPERE®and any potential adverse effects on the breastfed infant from XIPERE®. There are no data on the effects of XIPERE®on milk production.

8.4 Pediatric Use

Safety and effectiveness of XIPERE®in pediatric patients have not been established.

8.5 Geriatric Use

No overall differences in safety or effectiveness have been observed between elderly and younger patients following XIPERE®administration.

11 DESCRIPTION

XIPERE®is a sterile, injectable suspension of triamcinolone acetonide, a synthetic corticosteroid for suprachoroidal use with the SCS Microinjector®. Each mL of the aqueous suspension contains 40 mg of triamcinolone acetonide with 0.55% (weight/volume [w/v]) sodium chloride for tonicity, 0.5% (w/v) carboxymethylcellulose sodium, and 0.02% (w/v) polysorbate 80. It also contains potassium chloride, calcium chloride (dihydrate) and magnesium chloride (hexahydrate) as isotonicity agents, sodium acetate trihydrate(3.51 mg), sodium citrate dihydrate(1.53 mg), and water for injection. Hydrochloric acid may be used to adjust pH to a target value of 6.5. XIPERE®does not contain an anti-microbial preservative.

The chemical name for triamcinolone acetonide is 9-fluoro-11β,16ɑ,17,21-tetrahydroxypregna-1,4-diene-3,20-dione cyclic 16,17-acetal with acetone. Its chemical structure is:

Molecular weight 434.50; molecular formula C24H31FO6

Triamcinolone acetonide occurs as a white to cream-colored, crystalline powder having not more than a slight odor and is practically insoluble in water and very soluble in alcohol.

XIPERE®is provided as an injectable suspension in a single-dose glass vial with a rubber stopper and an aluminum seal. The SCS Microinjector®is a piston syringe and a needle approximately 1 mm in length (900-µm and 1100-µm needles are included) for conducting the suprachoroidal injection.

12 CLINICAL PHARMACOLOGY

12.1 Mechanism of Action

Triamcinolone acetonide is a synthetic glucocorticoid (glucocorticoids are often referred to as corticosteroids) with immunosuppressive and anti-inflammatory activity. The primary mechanism of action for triamcinolone acetonide is as a corticosteroid hormone receptor agonist.

12.3 Pharmacokinetics

In animal studies, data demonstrated that suprachoroidal injections resulted in larger amounts in total of triamcinolone acetonide found in the sclera, choroid, retinal pigment epithelial and retina, than with intravitreal injections of triamcinolone acetonide. Lower amounts of triamcinolone acetonide were found in the anterior segment and lens as compared to intravitreal injections of triamcinolone acetonide.

Plasma triamcinolone acetonide concentrations were evaluated in 19 patients with dosing of 4 mg XIPERE®at Day 0 and Week 12. Plasma triamcinolone acetonide concentrations in all 19 patients were below 100 pg/mL at Week 4, 12, and 24 (concentrations ranged from < 10 pg/mL [LLOQ (lower limit of quantitation) of the assay] to 88.9 pg/mL), with the exception of one patient with a value of 243.4 pg/mL prior to the second dose at Week 12.

13 NONCLINICAL TOXICOLOGY

13.1 Carcinogenesis, Mutagenesis, Impairment of Fertility

Carcinogenesis

No information is available on the carcinogenic potential of triamcinolone acetonide.

Mutagenesis

No information is available on the mutagenic potential of triamcinolone acetonide.

Fertility

No information is available on the effect of triamcinolone acetonide on fertility.

14 CLINICAL STUDIES

The efficacy of XIPERE®was assessed in a 6-month, randomized, multicenter, double-masked, sham-controlled study in patients with macular edema associated with anterior-, intermediate-, posterior-, or pan-uveitis. Patients were treated at baseline and Week 12.

The primary efficacy endpoint was the proportion of patients in whom best corrected visual acuity (BCVA) had improved by ≥ 15 letters from baseline after 24 weeks of follow-up (Table 2).

Table 2: Number of Patients with ≥ 15 Letters Improvement from Baseline at Week 24
Patients Who Gained ≥ 15 Letters from Baseline at Week 24 | XIPERE® (N = 96) | Control (N = 64)
n (%) | 45 (47%) | 10 (16%)
Estimated Difference (95% CI) | 31% (15%, 46%)
CMH p-value* | < 0.01
*The p-value was based on a Cochran Mantel Haenszel test for general association between treatment and response with stratification by country.

A statistically significantly greater proportion of patients treated with XIPERE®achieved a ≥ 15-letter improvement in BCVA than control patients (p < 0.01) at Week 24.

BCVA mean change from baseline at different visits is shown in Figure 1. Central subfield retinal thickness (CST) mean change from baseline at different visits is shown in Figure 2.

Figure 1: Mean Change from Baseline in BCVA

Figure 2: Mean Change from Baseline in CST

16 HOW SUPPLIED/STORAGE AND HANDLING

XIPERE®is supplied with the following sterile components for administration, sealed in a Tyvek covered tray, and one single-dose glass vial, in a carton with a package insert (NDC 24208-040-40):

- One SCS Microinjector®syringe with vial adapter attached
- One 30-G x 900-µm needle
- One 30-G x 1100-µm needle
- One single-dose vial of triamcinolone acetonide injectable suspension 40 mg/mL (NDC 24208-040-41)

Storage:Store at 15°C to 25°C (59°F to 77°F); do not freeze. The drug vial should be protected from light by storing in the carton. Discard unused portion.

17 PATIENT COUNSELING INFORMATION

Corticosteroid-Related Effects

Advise patients that they may develop elevated intraocular pressure following treatment, which may need to be managed with medication or surgery.

When to Seek Physician Advice

Advise patients that if the eye becomes red, sensitive to light, painful, or develops a change in vision, they should seek immediate care from an ophthalmologist.

Distributed by:

Bausch & Lomb Americas Inc.

Bridgewater, NJ 08807 USA

Patented. See https://patents.bausch.com for US patent information.

XIPERE®, SCS®, and SCS Microinjector®are trademarks of Clearside Biomedical, Inc. used under license.

© 2025 Bausch & Lomb Incorporated or its affiliates

9772102

PACKAGE/LABEL PRINCIPAL DISPLAY PANEL

NDC24208-040-40

XIPERE®

(triamcinolone acetonide

injectable suspension) 40 mg/mL

For suprachoroidal use

Carton contains:

• One single-dose glass vial of triamcinolone acetonide

injectable suspension 40 mg/mL

• One SCS Microinjector® syringe with

vial adapter attached

• One 30-G x 900-μm needle

• One 30-G x 1100-μm needle

• One package insert

Rx only

Store at 15°C to 25°C

(59°F to 77°F).

Do not freeze.

Protect from light.

BAUSCH + LOMB

9771902